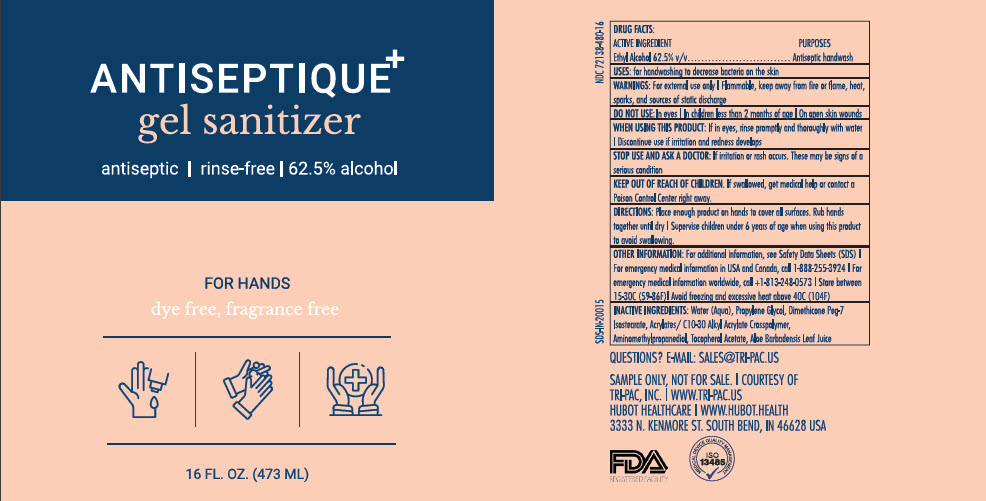 DRUG LABEL: Antiseptique
NDC: 72138-480 | Form: GEL
Manufacturer: Hubot Healthcare LLC
Category: otc | Type: HUMAN OTC DRUG LABEL
Date: 20200318

ACTIVE INGREDIENTS: ALCOHOL 62.5 mL/100 mL
INACTIVE INGREDIENTS: Water; Propylene Glycol; AMINOMETHYLPROPANOL; Dimethicone PEG-7 Isostearate; CARBOMER INTERPOLYMER TYPE A (ALLYL SUCROSE CROSSLINKED); Tocopherol; Aloe Vera Leaf

Antiseptique

Drug Facts

Active ingredient

Ethyl Alcohol 62.5% w/w

Purposes

Antiseptic handwash

Uses

for handwashing to decrease bacteria on the skin

Warnings

- For external use only
- Flammable, keep away from fire or flame, heat, sparks, and sources of static discharge

Do not use

- In eyes

When using this product

- If in eyes, rinse promptly and thoroughly with water
- Discontinue use if irritation and redness develops

Stop use and ask a doctor if skin irritation or redness occurs or persists for more than 72 hours.

Keep out of reach of children. If swallowed, get medical help or contact a Poison Control Center right away.

Directions

- Apply product onto hands, spread thoroughly and rub dry

Other Information

- For additional information, see Safety Data Sheets (SDS)
- For emergency medical information in USA and Canada, call 1-888-255-3924
- For emergency medical information worldwide, call 1-813-248-0573

Inactive Ingredients

water (aqua), propylene glycol, dimethicone PEG-7 Isostearate, acrylates/ C10-30 Alkyl Acrylate Crosspolymer, aminomethylpropanediol, tocopherol acetate, aloe barbadensis leaf juice

Questions?

Call 1-855-CLEAN-55 (253-2655)

PRINCIPAL DISPLAY PANEL - 473 ML Bottle Label

ANTISEPTIQUE^+
gel sanitizer

antiseptic | rinse-free | 62.5% alcohol

FOR HANDS
dye free, fragrance free

16 FL. OZ. (473 ML)